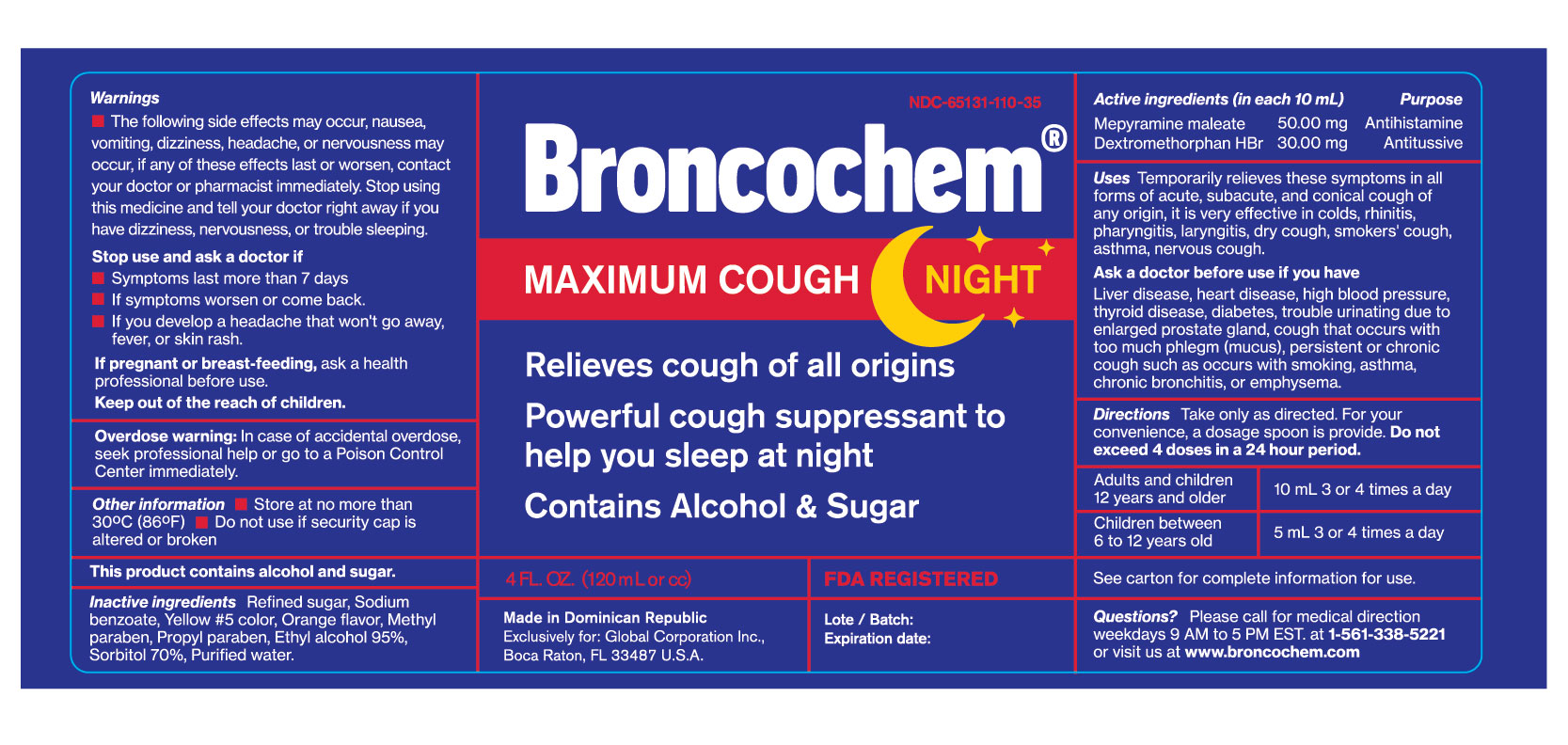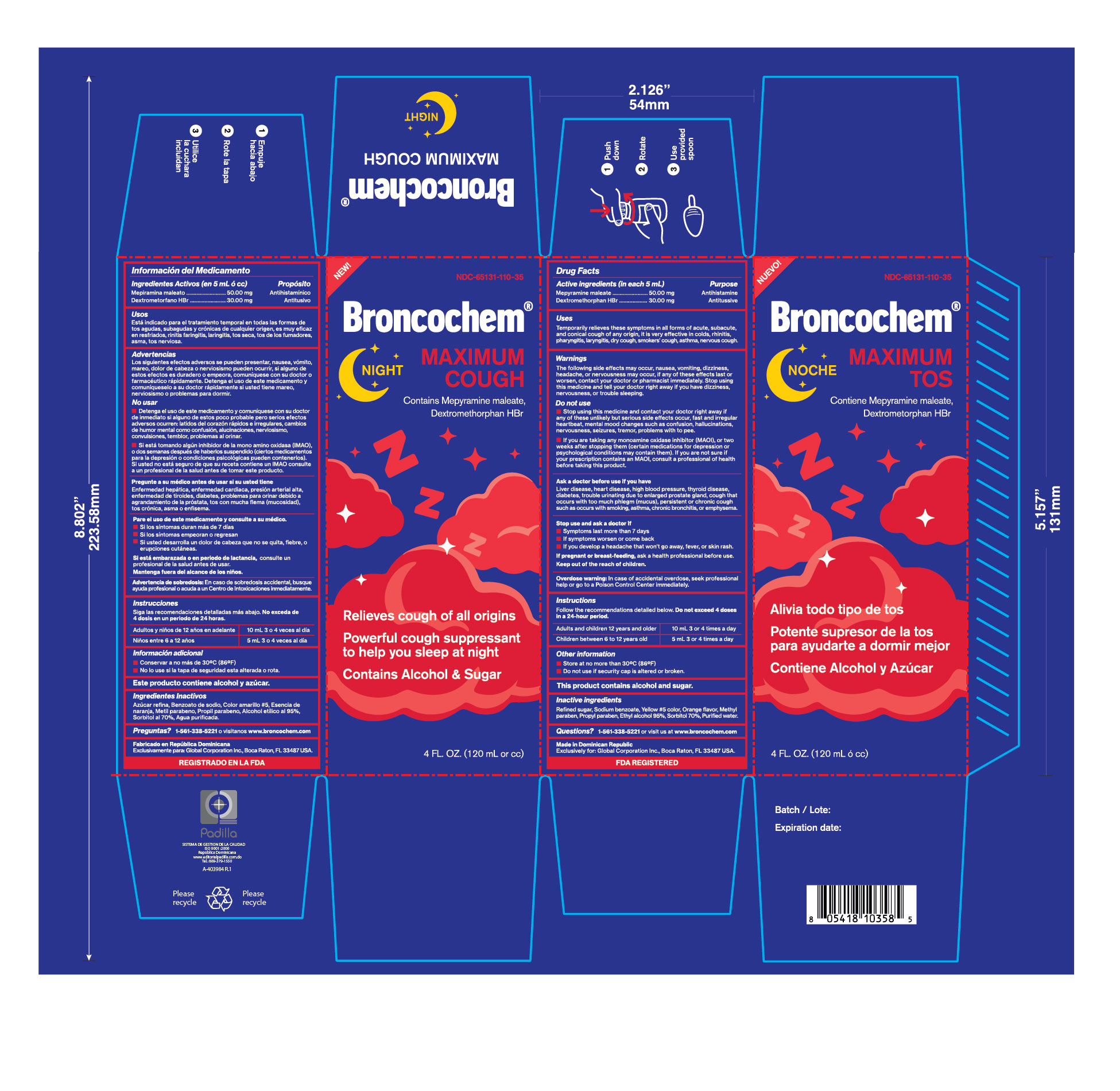 DRUG LABEL: BRONCOCHEM
NDC: 65131-110 | Form: SYRUP
Manufacturer: LABORATORIO MAGNACHEM INTERNATIONAL SRL
Category: otc | Type: HUMAN OTC DRUG LABEL
Date: 20250323

ACTIVE INGREDIENTS: DEXTROMETHORPHAN HYDROBROMIDE 30 mg/5 mL; PYRILAMINE MALEATE 50 mg/5 mL
INACTIVE INGREDIENTS: SUGARCANE 2.65 mg/5 mL; SODIUM BENZOATE 10 mg/5 mL; FD&C YELLOW NO. 5 0.25 mg/5 mL; ORANGE OIL 0.833 mg/5 mL; METHYLPARABEN SODIUM 5 mg/5 mL; PROPYLPARABEN SODIUM 1.5 mg/5 mL; ALCOHOL 95% 0.25 mL/5 mL; SORBITOL SOLUTION 70% 0.083 mL/5 mL; water 5 mL/5 mL

Broncochem Maximum Cough Night

Warnings

The following side effects may occur, nausea, vomiting, dizziness, headache, or nervousness may occur, if any of these effects last or worsen, contact your doctor or pharmacist immediately. Stop using this medicine and tell your doctor right away if you have dizziness, nervousness, or trouble sleeping.

OTC-PURPOSE SECTION

Antitussive

Antihistamine

OTC - Active Ingredient Section

Dextromethorphan HBr

Mepyramine maleate

Uses

Temporarily relieves these symptoms in all formsof acute, subacute, and cronical cough of any origin, it is very effective in colds, rhinitis, pharyngitis, laryngitis, dry cough, smokers cough, ashma, nervous cough.

Do Not Use

Stop using this medicine and contact your doctor right away if any of these unlikely but serious side effects occur, fast and irregular heartbeat, mental mood changes such as confusion, hallucinations, nervousness, seizures, tremor, problems with to pee.

If you are taking any monoamine oxidase inhibitor (MAOI), or two weeks after stopping them (certain medications for depression or psycological conditions may contain them). If you are not sure if your prescription contains an MAOI, coinsult a professional of health before taking this product.

Ask a doctor/pharmacist

Ask a doctor before use if yoy have

Liver disease, heart disease, high blood pressure, thyroid disease, diabetes, trouble urinating due to enlarged prostate gland, cough that occurs with too much phlegm (mucus), presistent or chronic cough such as occurs with smoking, asthma, chronic bronchitis, or emphysema.

Stop use and ask a doctor if

Symptoms last more than 7 days, symptoms worsen or come back, you develop a headache that wont go away, fever, or skin rash. If pregnant or breast-feeding ask a health professional before use.

Keep Out of the Reach of Children

In case of accidental overdose, seek professional help or go to poison control center immediately.

Dosage and Administration

Do not exceed 4 doses in a 24 hour period.

Adult and children 12 years and older: 10 mL 3-4 times a day.

Children 6 to under 12 years old: 5 mL 3-4 times a day.

Inactive Ingredient

Sugar, Sodium Benzoate, FD&C Yellow #5, Orange flavor, MEthyl paraben, Propyl paraben, ethyl alcohol 95%, Sorbitol 70%, Purified water.